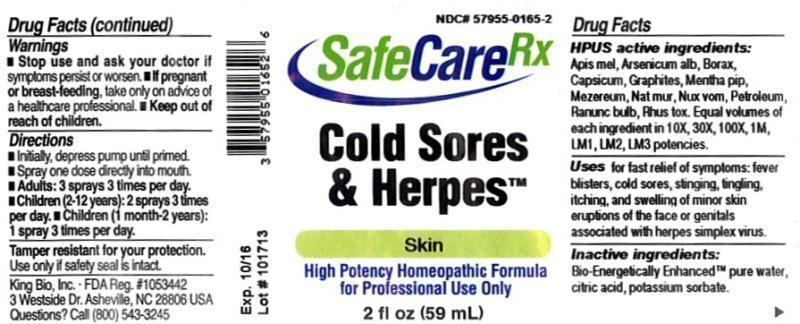 DRUG LABEL: Colds Sores and Herpes
NDC: 57955-0165 | Form: LIQUID
Manufacturer: King Bio Inc
Category: homeopathic | Type: HUMAN OTC DRUG LABEL
Date: 20140417

ACTIVE INGREDIENTS: APIS MELLIFERA 10 [hp_X]/59 mL; ARSENIC TRIOXIDE 10 [hp_X]/59 mL; SODIUM BORATE 10 [hp_X]/59 mL; CAPSICUM 10 [hp_X]/59 mL; GRAPHITE 10 [hp_X]/59 mL; MENTHA PIPERITA 10 [hp_X]/59 mL; DAPHNE MEZEREUM BARK 10 [hp_X]/59 mL; SODIUM CHLORIDE 10 [hp_X]/59 mL; STRYCHNOS NUX-VOMICA SEED 10 [hp_X]/59 mL; KEROSENE 10 [hp_X]/59 mL; RANUNCULUS BULBOSUS 10 [hp_X]/59 mL; TOXICODENDRON PUBESCENS LEAF 10 [hp_X]/59 mL
INACTIVE INGREDIENTS: WATER; CITRIC ACID MONOHYDRATE; POTASSIUM SORBATE

Cold Sores and Herpes™

ACTIVE INGREDIENT

Drug Facts__________________________________________________________________________________________________________

HPUS active ingredients: Apis mellifica, Arsenicum album, Borax, Capsicum annuum, Graphites, Mentha piperita, Mezereum, Natrum muriaticum, Nux vomica, Petroleum, Ranunculus bulbosus, Rhus toxicodendron. Equal volumes of each ingredient in 10X, 30X, 100X, 1M, LM1, LM2, LM3 potencies.

INDICATIONS AND USAGE

Uses for fast relief of symptoms: fever blisters, cold sores, stinging, tingling, itching, and swelling of minor skin eruptions of the face or genitals associated with herpes simplex virus.

Inactive Ingredients:

Bio-Energetically Enhanced™ pure water, citric acid and potassium sorbate.

Warnings

- Stop use and ask your doctor if symptoms persist or worsen.
- If pregnant or breast-feeding, take only on advice of a healthcare professional.

- Keep out of reach of children.

Directions

- Initially, depress pump until primed.
- Spray one dose directly into mouth.
- Adults: 3 sprays 3 times per day.
- Children (2-12 years): 2 sprays 3 times per day.
- Children (1 month-2 years): 1 spray 3 times per day.

OTHER SAFETY INFORMATION

Tamper resistant for your protection. Use only if safety seal is intact.

PURPOSE

Uses for fast relief of symptoms:

- fever blisters
- cold sores
- stinging, tingling, itching, and swelling of minor skin eruptions of the face or genitals associated with herpes simplex virus.